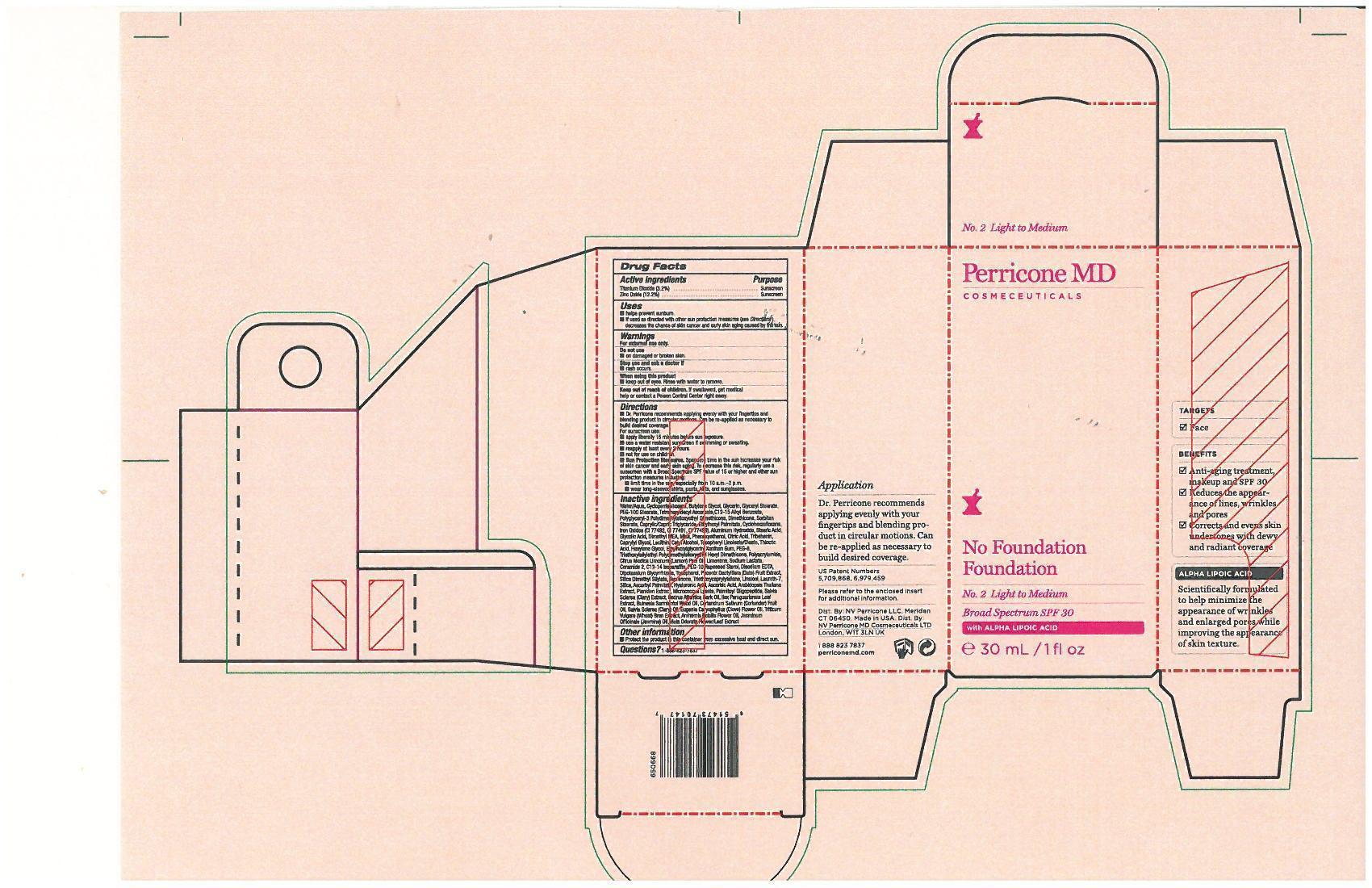 DRUG LABEL: No Foundation Foundation No.2 Light to Medium
NDC: 62742-4066 | Form: CREAM
Manufacturer: Allure Labs, Inc.
Category: otc | Type: HUMAN OTC DRUG LABEL
Date: 20140414

ACTIVE INGREDIENTS: ZINC OXIDE 122 mg/1 mL; TITANIUM DIOXIDE 32 mg/1 mL
INACTIVE INGREDIENTS: WATER; CYCLOMETHICONE 5; BUTYLENE GLYCOL; GLYCERIN; GLYCERYL MONOSTEARATE; POLYOXYL 100 STEARATE; TETRAHEXYLDECYL ASCORBATE; C12-15 ALKYL BENZOATE; SORBITAN MONOSTEARATE; MEDIUM-CHAIN TRIGLYCERIDES; ETHYLHEXYL PALMITATE; CYCLOMETHICONE 6; FERRIC OXIDE RED; FERRIC OXIDE YELLOW; FERROSOFERRIC OXIDE; GLYCOLIC ACID; 2-(DIETHYLAMINO)ETHANOL; MICA; PHENOXYETHANOL; CITRIC ACID MONOHYDRATE; TRIBEHENIN; CAPRYLYL GLYCOL; LECITHIN, SOYBEAN; CETYL ALCOHOL; ALPHA-TOCOPHEROL, D-; ALPHA LIPOIC ACID; DIMETHICONE; HEXYLENE GLYCOL; ETHYLHEXYLGLYCERIN; XANTHAN GUM; POLYETHYLENE GLYCOL 400; CYCLOMETHICONE; ACRYLAMIDE; LEMON OIL; LIMONENE, (+)-; SODIUM LACTATE; ALUMINUM HYDROXIDE; STEARIC ACID; C13-14 ISOPARAFFIN; EDETATE DISODIUM; GLYCYRRHIZINATE DIPOTASSIUM; ALPHA-TOCOPHEROL; DATE; TEPRENONE; LINALOOL, D-; LAURETH-7; SILICON DIOXIDE; ASCORBYL PALMITATE; HYALURONIC ACID; ASCORBIC ACID; CLARY SAGE; ILEX PARAGUARIENSIS LEAF; GUAIAC OIL; CORIANDER OIL; CLOVE OIL; WHEAT BRAN; CHAMAEMELUM NOBILE FLOWER; JASMINUM OFFICINALE FLOWER; VIOLA ODORATA

Drug Facts

PURPOSE:

Sunscreen

USES:

Helps prevent sunburn

If used as directed with other sun protection measures (see directions) decreases the chance of skin cancer and early skin aging caused by the sun.

WARNINGS:

- For external use only

WHEN USING THIS PRODUCT:

- Keep out of eyes. Rinse with water to remove.

STOP USE AND ASK A DOCTOR IF

- Rash occurs.

KEEP OUT OF REACH OF CHILDREN

If swallowed, get medical help or contact a Poison Control Center right away.

DIRECTIONS:

- Dr. Perricone recommends applying evenly with your fingertips and blending product in circular motions. Can be re-applied as necessary to build desired coverage.
- use liberally 15 minutes before sun exposure
- use a water resistant sunscreen if swimming or sweating
- reapply at least evry 2 hours
- Not for use on children.
- Sun Protection Measures. Spending time in the sun increases your risk of skin cancer and early skin aging. To decrease the risk, regularly use a sunscreen with a Broad Spectrun SPF value of 15 or higher and other sun protection measures including:
- Limit time in the sun, especially from 10:00am -2pm.
- wear long-sleeved shirts, pants, hats and sunglasses.

Other Information:

- Protect the production this container from excessive heat and direct sun.

INACTIVE INGREDIENTS:

Aqua (Water), Cyclopentasiloxane, Butylene Glycol, Glycerin, Glyceryl Stearate, PEG-100 Stearate, Tetrahexyldecyl Ascorbate, C12-15 Alkyl Benzoate, Polyglyceryl-3 Polydimethylsiloxyethyl Dimethicone,Dimethicone, Sorbitan Stearate, Caprylic/Capric Triglyceride, Ethylhexyl Palmitate, Cyclohexasiloxane, Iron Oxides (CI77492, CI77491, CI77499), Aluminum Hydroxide, Stearic AcidGlycolic Acid, Dimethyl MEA (DMAE), Mica, Phenoxyethanol, Citric Acid, Tribehenin, Caprylyl Glycol, Lecithin, Cetyl Alcohol, Tocopheryl Linoleate/Oleate, Thioctic Acid (Alpha-Lipoic Acid), Hexylene Glycol, Ethylhexylglycerin, Xanthan Gum, PEG-8, Triethoxysilylethyl Polydimethylsilxyethyl Hexyl Dimethicone, Polyacrylamide, Citrus Medica Limonum (Lemon) Peel Oil, Limonene, Sodium Lactate, Ceramide-2, Aluminum Hydroxide,C13-14 Isoparaffin, PEG-10 Rapeseed Sterol, Disodium EDTA, Dipotassium Glycyrrhizate, Tocopherol, Phoenix Dactylifera (Date) Fruit Extract, Silica Dimethyl Silylate, Teprenone, Triethoxycaprylylsilane, Linalool, Laureth-7, Silica, Ascorbyl Palmitate, Hyaluronic Acid, Ascorbic Acid, Arabidopsis Thaliana Extract, Plankton Extract, Micrococcus Lysate, Palmitoyl Oligopeptide, Salvia Sclarea (Clary) Extract, Cedrus Atlantica Bark Oil, Ilex Paraguariensis Leaf Extract, Bulnesia SarmientoiWood Oil, Coriandrm Sativum (Coriander) Fruit Oil, Salvia Sclarea (Clary) Oil, Eugenia Caryophyllus (Clove) Flower Oil, Triticum Vulgare (Wheat) Bran Extract, Anthemis Nobilis Flower Oil, Jasminum Officinale (Jasmine) Oil, Viola Odorata Flower/Leaf Extract.

PACKAGE LABEL

DISTRIBUTOR (US):

NV Perricone LLC,

Meriden CT 06450.

DISTRIBUTOR (UK):

NV Perricone MD Cosmeceuticals LTD

London, W1T 3LN UK

www.perriconemd.com

1 888 823 7837

IMAGE OF THE PRODUCT: